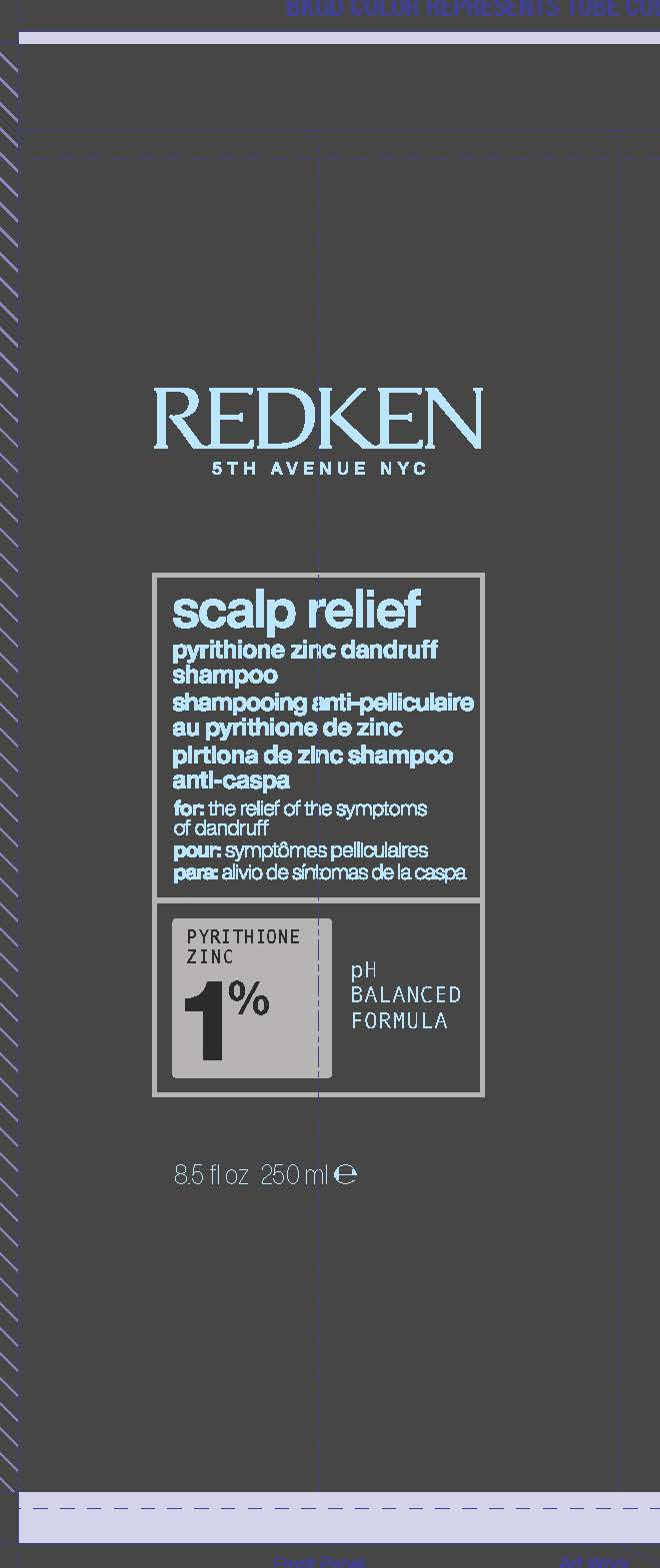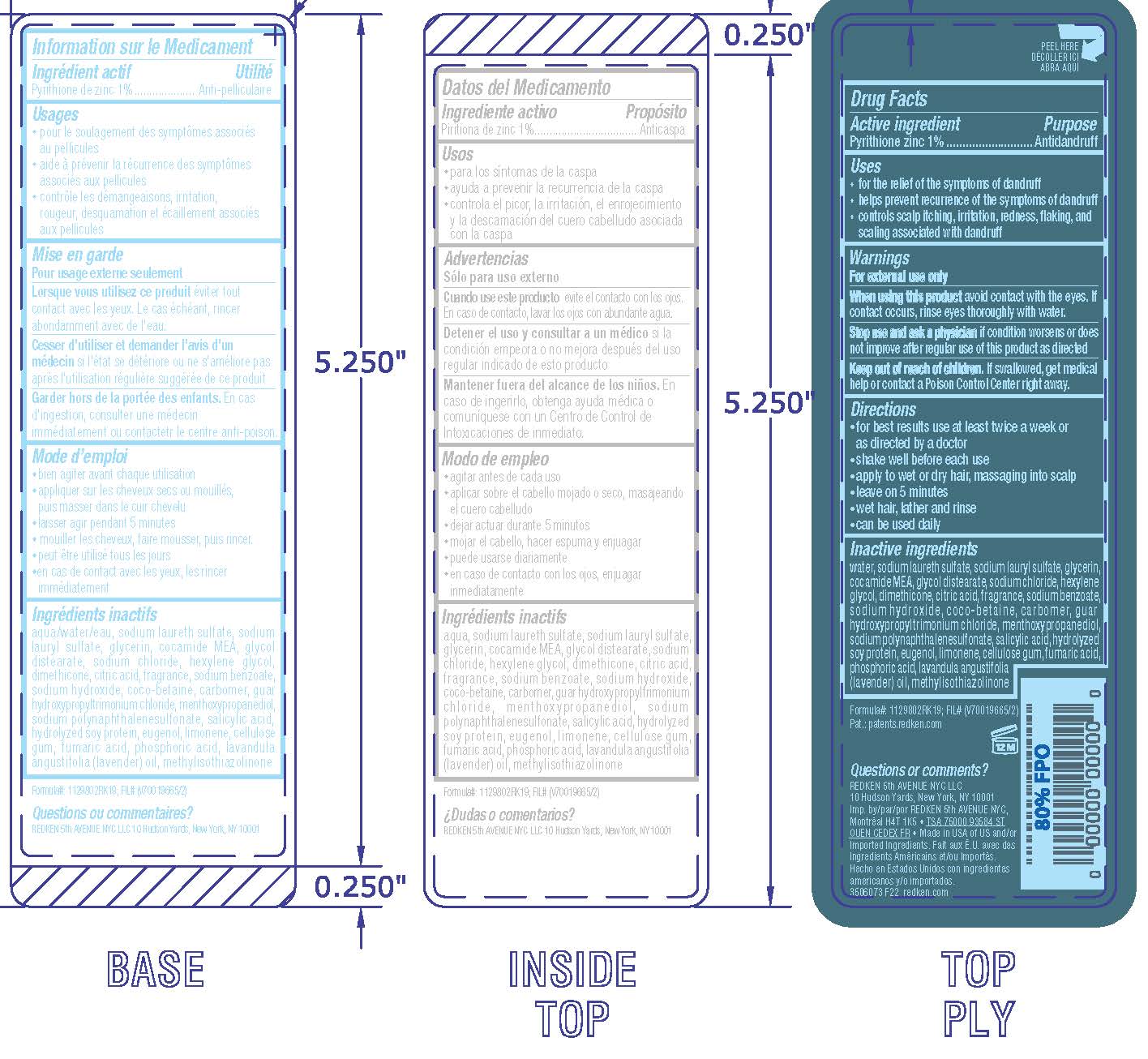 DRUG LABEL: Redken 5th Avenue NYC Scalp Relief Dandruff Control
NDC: 49967-795 | Form: SHAMPOO
Manufacturer: L'Oreal USA Products Inc
Category: otc | Type: HUMAN OTC DRUG LABEL
Date: 20231211

ACTIVE INGREDIENTS: PYRITHIONE ZINC 10 mg/1 mL
INACTIVE INGREDIENTS: WATER; SODIUM LAURETH SULFATE; SODIUM LAURYL SULFATE; GLYCERIN; COCO MONOETHANOLAMIDE; GLYCOL DISTEARATE; SODIUM CHLORIDE; HEXYLENE GLYCOL; DIMETHICONE; CITRIC ACID MONOHYDRATE; SODIUM BENZOATE; SODIUM HYDROXIDE; COCO-BETAINE; CARBOMER HOMOPOLYMER, UNSPECIFIED TYPE; GUAR HYDROXYPROPYLTRIMONIUM CHLORIDE (1.7 SUBSTITUENTS PER SACCHARIDE); 3-((L-MENTHYL)OXY)PROPANE-1,2-DIOL; SALICYLIC ACID; HYDROLYZED SOY PROTEIN (ENZYMATIC; 2000 MW); EUGENOL; LIMONENE, (+)-; CARBOXYMETHYLCELLULOSE SODIUM, UNSPECIFIED; EGG PHOSPHOLIPIDS; FUMARIC ACID; PHOSPHORIC ACID; LAVENDER OIL; METHYLISOTHIAZOLINONE; TOCOPHEROL

Drug Facts

Active ingredient

Pyrithione zinc 1%

Purpose

Antidandruff

Uses

- for the relief of the symptoms of dandruff
- helps prevent recurrence of the symptoms of dandruff
- controls scalp itching, irritation, redness, flaking and scaling associated with dandruff

Warnings

For external use only

When using this product

avoid contact with the eyes. If contact occurs, rinse eyes thoroughly with water.

Stop use and ask a physician if

condition worsens or does not improve after regular use

Keep out of reach of children.

If swallowed, get medical help or contact a Poison Control Center right away.

Directions

- for best results use at least twice a week or as directed by a physician
- shake well before each use
- apply to wet or dry hair, massaging into scalp
- leave on 5 minutes
- wet hair, lather and rinse
- can be used daily

Inactive ingredients

water, sodium laureth sulfate, sodium lauryl sulfate, glycerin, cocamide MEA, glycol distearate, sodium chloride, hexylene glycol, dimethicone, citric acid, fragrance, sodium benzoate, sodium hydroxide, coco-betaine, carbomer, guar hydroxypropyltrimonium chloride, menthoxypropanediol, sodium polynaphthalenesulfonate, salicylic acid, hydrolyzed soy protein, eugenol, limonene, cellulose gum, lecithin, fumaric acid, phosphoric acid, lavandula angustifolia (lavender) oil, methylisothiazolinone, tocopherol